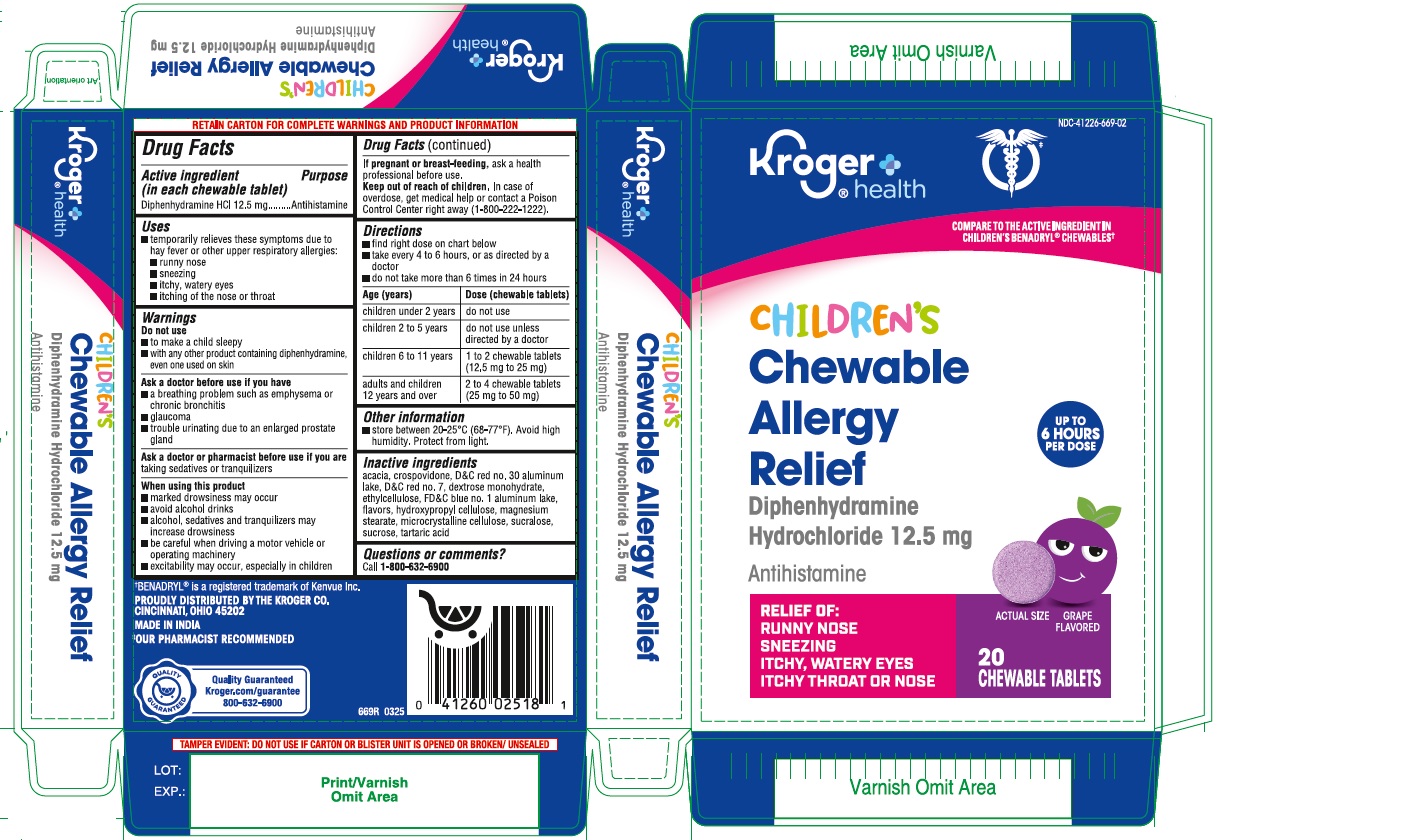 DRUG LABEL: Childrens Chewable Allergy Relief
NDC: 41226-669 | Form: TABLET, CHEWABLE
Manufacturer: KROGER COMPANY
Category: otc | Type: HUMAN OTC DRUG LABEL
Date: 20250814

ACTIVE INGREDIENTS: DIPHENHYDRAMINE HYDROCHLORIDE 12.5 mg/1 1
INACTIVE INGREDIENTS: ACACIA; D&C RED NO. 7; CROSPOVIDONE; MICROCRYSTALLINE CELLULOSE; SUCROSE; DEXTROSE MONOHYDRATE; FD&C BLUE NO. 1 ALUMINUM LAKE; SUCRALOSE; D&C RED NO. 30 ALUMINUM LAKE; ETHYLCELLULOSE; HYDROXYPROPYLCELLULOSE; MAGNESIUM STEARATE; TARTARIC ACID

Kroger Diphenhydramine Hydrochloride 12.5 mg Chewable Tablets - Childrens Grape Flavor

Active ingredient (in each chewable tablet)

Diphenhydramine HCl 12.5 mg

Purpose

Antihistamine

Uses

- temporarily relieves these symptoms due to hay fever or other upper respiratory allergies:

-runny nose
-sneezing
-itchy, watery eyes
-itching of the nose or throat

Warnings

Do not use

- to make a child sleepy
- with any other product containing diphenhydramine, even one used on skin

Ask a doctor before use if you have

- a breathing problem such as emphysema or chronic bronchitis
- glaucoma
- trouble urinating due to an enlarged prostate gland

Ask a doctor or pharmacist before use if you are taking sedatives or tranquilizers

When using this product

- marked drowsiness may occur
- avoid alcohol drinks
- alcohol, sedatives and tranquilizers may increase drowsiness
- be careful when driving a motor vehicle or operating machinery
- excitability may occur, especially in children

PREGNANCY OR BREAST FEEDING

If pregnant or breast-feeding, ask a health professional before use.

Keep out of reach of children. In case of overdose, get medical help or contact a Poison Control Center right away (1-800-222-1222).

Directions

- find right dose on chart below
- take every 4 to 6 hours, or as directed by a doctor
- do not take more than 6 times in 24 hours

Age (years) | Dose (chewable tablets)
children under 2 years | do not use
children 2 to 5 years | do not use unless directed by a doctor
children 6 to 11 years | 1 to 2 chewable tablets (12.5 mg to 25 mg)
adults and children 12 years and over | 2 to 4 chewable tablets (25 mg to 50 mg)

Other information

- store between 20-25°C (68-77°F). Avoid high humidity. Protect from light.

Inactive ingredients

acacia, crospovidone, D&C red no. 30 aluminum lake, D&C red no. 7, dextrose monohydrate, ethylcellulose, FD&C blue no. 1 aluminum lake, flavors, hydroxypropyl cellulose, magnesium stearate, microcrystalline cellulose, sucralose, sucrose, tartaric acid

Questions or comments?

Call 1-800-632-6900